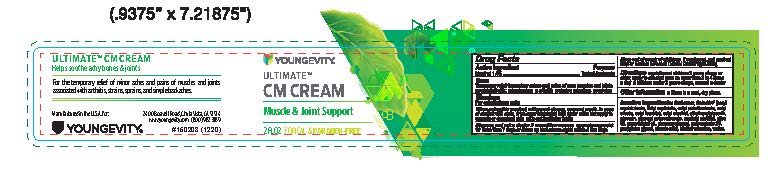 DRUG LABEL: Topical Analgesic
NDC: 80986-101 | Form: CREAM
Manufacturer: Youngevity International Inc.
Category: otc | Type: HUMAN OTC DRUG LABEL
Date: 20251022

ACTIVE INGREDIENTS: MENTHOL 1.4 g/100 g
INACTIVE INGREDIENTS: CETYL TALLOWATE; CARBOMER HOMOPOLYMER, UNSPECIFIED TYPE; STEARIC ACID; OLIVE OIL; PEPPERMINT OIL; POLYSORBATE 20; ETHYLHEXYLGLYCERIN; PHENOXYETHANOL; TROLAMINE; GLYCERYL STEARATE SE; CETYL ALCOHOL; WATER; GLYCERIN; PROPYLENE GLYCOL

CM Cream

Active Ingredient

Menthol 1.4%, Purpose: Topical Analgesic

Purpose

Topical Analgesic

Uses

Temporary relief on minor aches and pains of sore muscles and joints associated with:

- Backaches
- arthritis
- strains
- bruises
- sprains

Warnings

For external use only.

Stop use and ask a doctor if

- condition worsens
- symptoms persists for more than 7 day or clears up and occurs again within a few days

When using this product

- Keep out of eyes, ears, and mouth
- In case of contact with eyes, rinse eyes thoroughly with water
- Do not apply to wounds or damaged skin
- Do not bandage tightly

Keep out of reach of children

If swallowed, get medical help or contact a Poison Control Center right away.

Directions

adults and children 2 years of age or older, apply to affected area no more than 3 to 4 times a day.

children under 2 years of age, consult a doctor.

Other information

Store in a cool, dry place

Inactive Ingredient

Carbomer, celadrin (cetyl myristoleate, cetyl myristate, cetyl palmitaoleate, cetyl oleate, cetyl laurate), cetyl alcohol, ethylhexylglycerin, glycerin, glyceryl monostearate, myristyl alcohol, olive oil, peppermint oil, phenoxyethanol, polysorbate 20, propylene glycol, stearic acid, triethanolamine, water

PDP

Ultimate CM Cream Muscle and Joint Support 2 fl oz